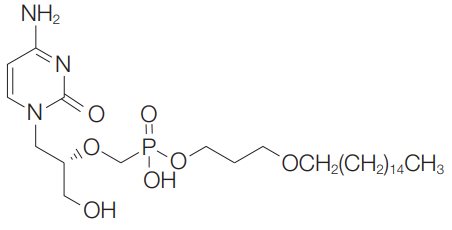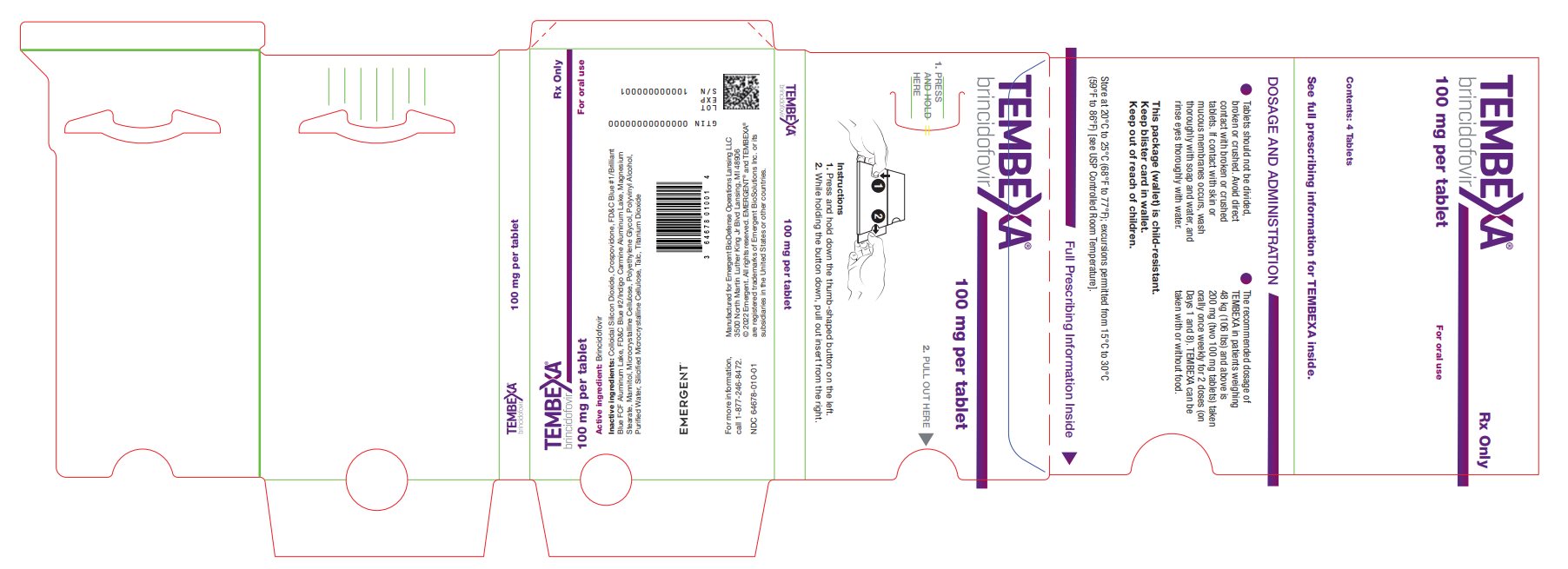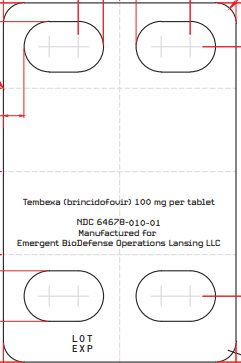 DRUG LABEL: Tembexa
NDC: 64678-010 | Form: TABLET, FILM COATED
Manufacturer: Emergent BioDefense Operations Lansing LLC
Category: prescription | Type: HUMAN PRESCRIPTION DRUG LABEL
Date: 20230224

ACTIVE INGREDIENTS: BRINCIDOFOVIR 100 mg/1 1
INACTIVE INGREDIENTS: MICROCRYSTALLINE CELLULOSE; CROSPOVIDONE, UNSPECIFIED; MANNITOL; SILICON DIOXIDE; MAGNESIUM STEARATE; WATER; FD&C BLUE NO. 1; FD&C BLUE NO. 2; POLYETHYLENE GLYCOL, UNSPECIFIED; POLYVINYL ALCOHOL, UNSPECIFIED; TALC; TITANIUM DIOXIDE

HIGHLIGHTS OF PRESCRIBING INFORMATION

These highlights do not include all the information needed to use TEMBEXA® safely and effectively. See full prescribing information for TEMBEXA.
TEMBEXA (brincidofovir) tablets, for oral use
TEMBEXA (brincidofovir) oral suspension
Initial U.S. Approval: 1996

WARNING: INCREASED RISK FOR MORTALITY WHEN USED FOR LONGER DURATION

See full prescribing information for complete boxed warning.

An increased incidence of mortality was seen in TEMBEXA-treated subjects compared to placebo-treated subjects in a 24-week clinical trial when TEMBEXA was evaluated in another disease [see Warnings and Precautions (5.1)].

1 INDICATIONS AND USAGE

TEMBEXA is an orthopoxvirus nucleotide analog DNA polymerase inhibitor and is indicated for the treatment of human smallpox disease in adult and pediatric patients, including neonates. (1.1)

Limitations of Use:

- TEMBEXA is not indicated for the treatment of diseases other than human smallpox disease. (1.2)
- The effectiveness of TEMBEXA for treatment of smallpox disease has not been determined in humans because adequate and well-controlled field trials have not been feasible, and inducing smallpox disease in humans to study the drug’s efficacy is not ethical. (1.2)
- TEMBEXA efficacy may be reduced in immunocompromised patients based on studies in immune deficient animals. (1.2)

2 DOSAGE AND ADMINISTRATION

- Testing: Before initiation and during treatment with TEMBEXA perform hepatic laboratory testing and pregnancy testing. (2.1)
- See full prescribing information for details on important administration instructions. (2.2)
- Adult and pediatric patients weighing 48 kg or above: 200 mg (two 100 mg tablets or 20 mL oral suspension for patients who cannot swallow tablets) once weekly for 2 doses. (2.3)
- Adult and pediatric patients weighing 10 kg to less than 48 kg: 4 mg/kg oral suspension once weekly for 2 doses. (2.3)
- Pediatric patients weighing less than 10 kg: 6 mg/kg oral suspension once weekly for 2 doses. (2.3)

3 DOSAGE FORMS AND STRENGTHS

- Tablets: 100 mg (3)
- Oral Suspension: 10 mg/mL (3)

4 CONTRAINDICATIONS

None. (4)

5 WARNINGS AND PRECAUTIONS

- Elevations in Hepatic Transaminases and Bilirubin: May cause increases in serum transaminases (ALT or AST) and serum bilirubin. Monitor liver laboratory parameters before and during treatment. (5.2)
- Diarrhea and Other Gastrointestinal Adverse Events: Diarrhea and additional gastrointestinal adverse events including nausea, vomiting, and abdominal pain may occur. Monitor patients, provide supportive care, and if necessary, do not give the second and final dose of TEMBEXA. (5.3)
- Coadministration with Related Products: TEMBEXA should not be coadministered with intravenous cidofovir. (5.4)
- Embryo-fetal Toxicity: May cause fetal harm. Advise individuals of childbearing potential of the potential risk to the fetus and to use effective contraception. (5.5, 8.1, 8.3)
- Carcinogenicity: TEMBEXA should be considered a potential human carcinogen. Do not crush or divide TEMBEXA tablets. (5.6, 13.1)
- Male Infertility: Based on testicular toxicity in animal studies, TEMBEXA may irreversibly impair fertility in individuals of reproductive potential. (5.7, 8.3)

6 ADVERSE REACTIONS

Common adverse reactions (occurring in at least 2% of TEMBEXA-treated subjects) were diarrhea, nausea, vomiting, and abdominal pain. (6.1)

To report SUSPECTED ADVERSE REACTIONS, contact Emergent BioDefense Operations Lansing LLC at 1‑877-246-8472 or FDA at 1-800-FDA-1088 or www.fda.gov/medwatch.

7 DRUG INTERACTIONS

Concomitant use with OATP1B1 and 1B3 inhibitors increase TEMBEXA exposure which may increase TEMBEXA-associated adverse reactions. Consider alternative medication that are not OATP1B1 or 1B3 inhibitors. If concomitant use is necessary, increase monitoring for adverse reactions associated with TEMBEXA and postpone the dosing of OATP1B1 or 1B3 inhibitors at least 3 hours after TEMBEXA administration. (7.1)

8 USE IN SPECIFIC POPULATIONS

Lactation: Breastfeeding not recommended. (8.2)

FULL PRESCRIBING INFORMATION

WARNING: INCREASED RISK FOR MORTALITY WHEN USED FOR LONGER DURATION

An increased incidence of mortality was seen in TEMBEXA-treated subjects compared to placebo-treated subjects in a 24-week clinical trial when TEMBEXA was evaluated in another disease [see Warnings and Precautions (5.1)].

1 INDICATIONS AND USAGE

1.1 Treatment of Human Smallpox Disease

TEMBEXA® is indicated for the treatment of human smallpox disease caused by variola virus in adult and pediatric patients, including neonates.

1.2 Limitations of Use

TEMBEXA is not indicated for the treatment of diseases other than human smallpox disease [see Warnings and Precautions (5.1, 5.2)].

The effectiveness of TEMBEXA for the treatment of smallpox disease has not been determined in humans because adequate and well-controlled field trials have not been feasible, and inducing smallpox disease in humans to study the drug’s efficacy is not ethical [see Clinical Studies (14)].

TEMBEXA efficacy may be reduced in immunocompromised patients based on studies in immune deficient animals.

2 DOSAGE AND ADMINISTRATION

2.1 Testing Before Initiating and During Treatment with TEMBEXA

Perform hepatic laboratory testing in all patients before starting TEMBEXA and while receiving TEMBEXA, as clinically appropriate [see Warnings and Precautions (5.2) and Use in Specific Populations (8.7)].

Perform pregnancy testing before initiation of TEMBEXA in individuals of childbearing potential to inform risk [see Warnings and Precautions (5.5) and Use in Specific Populations (8.3)].

2.2 Important Administration Instructions

Avoid direct contact with broken or crushed tablets or oral suspension. If contact with skin or mucous membranes occurs, wash thoroughly with soap and water, and rinse eyes thoroughly with water [see Warnings and Precautions (5.6)].

TEMBEXA Tablets

TEMBEXA tablets can be taken on an empty stomach or with a low-fat meal (approximately 400 calories, with approximately 25% of calories from fat) [see Clinical Pharmacology (12.3)]. Swallow TEMBEXA tablets whole. Do not crush or divide TEMBEXA tablets.

TEMBEXA Oral Suspension

Take TEMBEXA oral suspension on an empty stomach [see Clinical Pharmacology (12.3)]. Shake oral suspension before use. Use an appropriate oral dosing syringe to correctly measure the total prescribed dose [see Patient Counseling Information (17)]. Discard unused portion after completion of 2 prescribed doses.

For patients who cannot swallow, TEMBEXA oral suspension can be administered by enteral tube (naso-gastric or gastrostomy tubes) as follows:

- Draw up prescribed dose with a calibrated catheter-tip syringe, and utilize this syringe to administer the dose via the enteral tube.
- Refill the catheter-tip syringe with 3 mL of water, shake, and administer the contents via the enteral tube.
- Flush with water before and after enteral administration.

2.3 Recommended Dosage

The recommended dosage of TEMBEXA in pediatric and adult patients is displayed in Table 1 [see Drug Interactions (7.1), Clinical Pharmacology (12.3) and Clinical Studies (14)].

Table 1: Recommended Dosage in Pediatric and Adult Patients
Patient’s Weight (kg) | TEMBEXA Oral Suspension; (10 mg/mL) | TEMBEXA Tablet; (100 mg)
Less than 10 kg | 6 mg/kg once weekly for 2 doses (on Days 1 and 8) | N/A
10 kg to less than 48 kg | 4 mg/kg once weekly for 2 doses (on Days 1 and 8) | N/A
48 kg and above | 200 mg (20 mL) once weekly for 2 doses (on Days 1 and 8) | 200 mg (two 100 mg tablets) once weekly for 2 doses (on Days 1 and 8)

3 DOSAGE FORMS AND STRENGTHS

Tablets

TEMBEXA tablets are blue, modified-oval shape, film-coated tablets debossed with BCV on one side and 100 on the other side. Each tablet contains 100 mg of brincidofovir.

Oral Suspension

TEMBEXA oral suspension is an aqueous based, preserved white to off-white opaque, lemon lime flavored suspension containing 10 mg/mL of brincidofovir.

4 CONTRAINDICATIONS

None.

5 WARNINGS AND PRECAUTIONS

5.1 Increased Risk for Mortality When Used for Longer Duration

TEMBEXA is not indicated for use in diseases other than human smallpox. An increase in mortality was observed in a randomized, placebo-controlled Phase 3 trial when TEMBEXA was evaluated in another disease. An increased risk in mortality is possible if TEMBEXA is used for a duration longer than at the recommended dosage on Days 1 and 8 [see Indications and Usage (1.2) and Dosage and Administration (2.3)].

Study 301 (CMX001-301) evaluated TEMBEXA versus placebo for the prevention of cytomegalovirus infection. A total of 303 subjects received TEMBEXA (100 mg twice weekly) and 149 subjects received matching placebo for up to 14 weeks. The primary endpoint was evaluated at Week 24. All-cause mortality at Week 24 was 16% in the TEMBEXA group compared to 10% in the placebo group. Safety and effectiveness of TEMBEXA have not been established for diseases other than human smallpox disease.

5.2 Elevations in Hepatic Transaminases and Bilirubin

Elevations in alanine aminotransferase (ALT), aspartate aminotransferase (AST), and total bilirubin have been observed, including cases of concurrent increases in ALT and bilirubin. During the first 2 weeks of TEMBEXA therapy in 392 subjects, ALT elevations >3x the upper limit of normal were reported in 7% of subjects and bilirubin elevations >2x the upper limit of normal were reported in 2% of subjects; these elevations in hepatic laboratory tests were generally reversible and did not require discontinuation of TEMBEXA [see Adverse Reactions (6.1) and Nonclinical Toxicology (13.2)]. Severe hepatobiliary adverse events including hyperbilirubinemia, acute hepatitis, hepatic steatosis, and venoocclusive liver disease have been reported in less than 1% of subjects.

Perform hepatic laboratory testing in all patients before starting TEMBEXA and while receiving TEMBEXA, as clinically appropriate. Monitor patients who develop abnormal hepatic laboratory tests during TEMBEXA therapy for the development of more severe hepatic injury. Consider discontinuing TEMBEXA if ALT levels remain persistently >10x the upper limit of normal. Do not give the second and final dose of TEMBEXA on Day 8 if ALT elevation is accompanied by clinical signs and symptoms of liver inflammation or increasing direct bilirubin, alkaline phosphatase, or International Normalized Ratio (INR) [see Adverse Reactions (6.1) and Drug Interactions (7.1)].

5.3 Diarrhea and Other Gastrointestinal Adverse Events

During the first 2 weeks of TEMBEXA therapy in 392 subjects, a composite term of diarrhea (all grade, all cause) occurred in 40% of TEMBEXA-treated subjects compared with 25% of subjects in the placebo control group. Treatment with TEMBEXA was discontinued in 5% of subjects for diarrhea (composite term) compared with 1% in the placebo control group. Additional gastrointestinal (GI) adverse events included nausea, vomiting, and abdominal pain; some of these adverse events required discontinuation of TEMBEXA [see Adverse Reactions (6.1) and Drug Interactions (7.1) and Nonclinical Toxicology (13.2)].

Monitor patients for GI adverse events including diarrhea and dehydration, provide supportive care, and if necessary, do not give the second and final dose of TEMBEXA.

5.4 Coadministration with Related Products

TEMBEXA should not be co-administered with intravenous cidofovir. Brincidofovir, a lipid-linked derivative of cidofovir, is intracellularly converted to cidofovir [see Clinical Pharmacology (12.3)].

5.5 Embryo-fetal Toxicity

Based on findings from animal reproduction studies, TEMBEXA may cause fetal harm when administered to pregnant individuals. TEMBEXA administration to pregnant rats and rabbits resulted in embryotoxicity, decreased embryo-fetal survival and/or structural malformations. These effects occurred in animals at systemic exposures less than the expected human exposure based on the recommended dose of TEMBEXA. Use an alternative therapy to treat smallpox during pregnancy, if feasible. Perform pregnancy testing in individuals of childbearing potential before initiation of TEMBEXA. Advise individuals of childbearing potential to avoid becoming pregnant and to use effective contraception during treatment with TEMBEXA and for at least 2 months after the last dose. Advise individuals of reproductive potential with partners of childbearing potential to use condoms during treatment with TEMBEXA and for at least 4 months after the last dose [see Use in Specific Populations (8.1, 8.3)].

5.6 Carcinogenicity

TEMBEXA is considered a potential human carcinogen. Mammary adenocarcinomas and squamous cell carcinomas occurred in rats at systemic exposures less than the expected human exposure based on the recommended dose of TEMBEXA [see Nonclinical Toxicology (13.1)]. Do not crush or divide TEMBEXA tablets. Avoid direct contact with broken or crushed tablets or oral suspension. If contact with skin or mucous membranes occurs, wash thoroughly with soap and water, and rinse eyes thoroughly with water [see How Supplied/Storage and Handling (16)].

5.7 Male Infertility

Based on testicular toxicity in animal studies, TEMBEXA may irreversibly impair fertility in individuals of reproductive potential [see Use in Specific Populations (8.3) and Nonclinical Toxicology (13.1)].

6 ADVERSE REACTIONS

The following clinically significant adverse reactions are described elsewhere in the labeling:

- Elevations in hepatic transaminases and bilirubin [see Warnings and Precautions (5.2)]
- Diarrhea and other GI adverse events [see Warnings and Precautions (5.3)]

6.1 Clinical Trials Experience

Because clinical trials are conducted under widely varying conditions, adverse reaction rates observed in the clinical trials of a drug cannot be directly compared to rates in the clinical trials of another drug and may not reflect the rates observed in practice.

The safety of TEMBEXA has not been studied in patients with smallpox disease.

The safety of TEMBEXA was evaluated in 392 adult subjects aged 18 to 77 years in Phase 2 and 3 randomized, placebo-controlled clinical trials. Of the subjects who received a 200 mg total weekly dose of TEMBEXA, 54% were male, 85% were White, 7% were Black/African American, 6% were Asian, and 10% were Hispanic or Latino. Twenty-one percent of subjects in the studies were age 65 or older. Of these 392 subjects, 85% received a 200 mg total weekly dose of TEMBEXA for at least 2 weeks.

Common Adverse Reactions

The most common adverse reactions (adverse events assessed as causally related by the investigator) experienced in the first 2 weeks of dosing with TEMBEXA were diarrhea and nausea. Adverse reactions that occurred in at least 2% of subjects in the TEMBEXA treatment group are shown in Table 2.

Table 2: Adverse Reactions (All Grades) Reported in ≥2% of Subjects
Adverse Reaction | TEMBEXA 200 mg; N=392; % | Placebo; N=208; %
Diarrheaa | 8 | 3
Nausea | 5 | 1
Vomitingb | 4 | 1
Abdominal painc | 3 | 2
Note: Only adverse reactions with onset in the first 2 weeks of treatment are presented.
a. Composite term includes: bowel movement irregularity, defecation urgency, diarrhea, fecal incontinence, and frequent bowel movements.
b. Composite term includes: vomiting and retching.
c. Composite term includes: abdominal discomfort, abdominal distention, abdominal pain, abdominal pain lower, abdominal pain upper, abdominal tenderness, and gastrointestinal pain.

Adverse Reactions Leading to Discontinuation of TEMBEXA

Fifteen subjects (4%) had their treatment with TEMBEXA discontinued due to adverse reactions. One subject had two adverse reactions; the other subjects had one reaction each. These adverse reactions were:

- Diarrhea (n=9)
- Nausea (n=3)
- Vomiting (n=1)

- Enteritis (n=1)
- ALT increased (n=1)
- Dyspepsia (n=1)

These adverse reactions were mild (Grade 1, n=1), moderate (Grade 2, n=7) or severe (Grade 3, n=8) in severity and resolved upon discontinuation of TEMBEXA.

Less Common Adverse Reactions

Clinically significant adverse reactions that were reported in <2% of subjects (and also occurred in 2 or more subjects) exposed to TEMBEXA and at rates higher than in subjects who received placebo are listed below:

- General and administration site: peripheral edema
- Metabolism and nutrition: decreased appetite
- Musculoskeletal and connective tissue: muscular weakness

- Nervous system: dysgeusia
- Skin and subcutaneous tissue: rash (includes rash, maculo-papular rash, pruritic rash)

Selected treatment-emergent laboratory values occurring during the first 2 weeks of treatment with TEMBEXA are presented in Table 3.

Table 3: Frequencies of Selected Laboratory Abnormalities
Laboratory Parameter Abnormalitya |  | TEMBEXA 200 mg; N=392 | Placebo; N=208
Alanine aminotransferase; (ALT)b | n | 382 | 203
Alanine aminotransferase; (ALT)b | Grade 2 (>3 to 5x ULN), (%) | 3 | 2
Alanine aminotransferase; (ALT)b | Grade 3 (>5 to 20x ULN), (%) | 2 | 1
Alanine aminotransferase; (ALT)b | Grade 4 (>20x ULN), (%) | 0 | 0
Aspartate aminotransferase; (AST)c | n | 380 | 201
Aspartate aminotransferase; (AST)c | Grade 2 (>3 to 5x ULN), (%) | 2 | 1
Aspartate aminotransferase; (AST)c | Grade 3 (>5 to 20x ULN), (%) | 1 | 0
Aspartate aminotransferase; (AST)c | Grade 4 (>20x ULN), (%) | 0 | 0
Total bilirubin | n | 382 | 203
Total bilirubin | Grade 2 (>1.5 to 3x ULN), (%) | 3 | 2
Total bilirubin | Grade 3 (>3 to 10x ULN), (%) | 1 | <1
Total bilirubin | Grade 4 (>10x ULN), (%) | 0 | 0
Serum creatinine | n | 383 | 205
Serum creatinine | Grade 2 (>1.5 to 3x ULN), (%) | 4 | 4
Serum creatinine | Grade 3 (>3 to 6x ULN), (%) | <1 | 0
Serum creatinine | Grade 4 (>6x ULN), (%) | 0 | 0
ULN = upper limit of normal
a. Frequencies are based on treatment-emergent laboratory abnormalities. Graded per Common Terminology Criteria for Adverse Events (CTCAE) version 4.03 toxicity grading criteria.
b. ALT >10x ULN occurred in one subject in the TEMBEXA group and no subjects in the placebo group.
c. No subjects reported AST >10x ULN.

Adverse Reactions in Pediatric Subjects

In 23 pediatric subjects aged 7 months to 17 years who received TEMBEXA in a randomized, placebo-controlled clinical trial, the adverse reactions and laboratory abnormalities observed with TEMBEXA were similar to adults [see Use in Specific Populations (8.4)].

7 DRUG INTERACTIONS

7.1 Effect of Other Drugs on TEMBEXA

Inhibitors for Organic Anion Transporting Polypeptide (OATP) 1B1 and 1B3

Concomitant use of TEMBEXA with OATP1B1 and 1B3 inhibitors (clarithromycin, cyclosporine, erythromycin, gemfibrozil, human immunodeficiency virus [HIV] and hepatitis C virus [HCV] protease inhibitors, rifampin [single dose]) increase brincidofovir AUC and Cmax which may increase TEMBEXA-associated adverse reactions [see Clinical Pharmacology (12.3)].

Where possible, consider alternative medications that are not OATP1B1 or 1B3 inhibitors. If concomitant use with TEMBEXA is necessary, increase monitoring for adverse reactions associated with TEMBEXA (elevations in transaminases and bilirubin, diarrhea, or other GI adverse events) [see Warnings and Precautions (5.2, 5.3)] and postpone the dosing of OATP1B1 or 1B3 inhibitors for at least 3 hours after TEMBEXA administration.

7.2 Vaccine Interactions

No vaccine-drug interaction studies have been performed in human subjects. Animal studies have indicated that coadministration of TEMBEXA at the same time as live smallpox vaccine (vaccinia virus) may reduce the immune response to the vaccine. It is also possible that TEMBEXA may reduce the immune response to replication-defective smallpox vaccine (modified vaccinia virus Ankara). The clinical impacts of these potential interactions on vaccine efficacy are unknown.

8 USE IN SPECIFIC POPULATIONS

8.1 Pregnancy

Risk Summary

Based on findings from animal reproduction studies, TEMBEXA may cause fetal harm when administered to pregnant individuals. Use an alternative therapy to treat smallpox during pregnancy, if feasible. There are no available data on the use of brincidofovir in pregnant individuals to evaluate for a drug-associated risk of major birth defects, miscarriage, and other adverse maternal and fetal outcomes. In animal reproduction studies, oral administration of brincidofovir to pregnant rats and rabbits during the period of organogenesis resulted in embryotoxicity and structural malformations. These effects occurred in animals at systemic exposures less than the expected human exposure based on the recommended dose of TEMBEXA (see Data).

The estimated background risk of major birth defects for the indicated population is unknown, and the estimated background risk of miscarriage for the indicated population is higher than the general population. All pregnancies have a background risk of birth defect, loss or other adverse outcomes. In the U.S. general population, the estimated background risk of major birth defects and miscarriage in clinically recognized pregnancies is 2% to 4% and 15% to 20%, respectively.

Data

Animal Data

In embryo-fetal development studies in rats and rabbits, pregnant animals were administered oral doses of brincidofovir up to 4.5 mg/kg/day from gestation days 7 to 20. Maternal toxicity in rats, characterized by decreases in food consumption and decreased body weight gain, was observed at doses of 1.5 and 4.5 mg/kg/day. These effects correlated with decreased fetal weights in rats given 4.5 mg/kg/day. Brincidofovir administration in rats was not associated with effects on intrauterine growth or survival at any dose, and there were no external malformations or developmental variations.

In rabbits, 4.5 mg/kg/day brincidofovir was associated with decreased maternal body weight and food consumption, decreased fetal body weight, increased late resorptions and morphological changes which included external, visceral and skeletal malformations and variations.

In the pre-/post-natal development study, administration of brincidofovir at doses of 0, 0.25, 1, and 4 mg/kg/day and 15 mg/kg twice weekly to pregnant rats from gestation day 7 to lactation day 20 resulted in pup toxicity at maternally toxic doses (4 mg/kg/day and 15 mg/kg twice weekly). Pup body weight and viability were decreased, and reproductive function of the pups was impaired as evidenced by a delay in sexual maturation, decreased testes and epididymal size, reduced mating and an increase in the number of days to mating as well as preimplantation loss.

All effects were observed at systemic exposures less than the expected human exposure based on the recommended dose of TEMBEXA.

8.2 Lactation

Risk Summary

Because of the potential for variola virus transmission through direct contact with the breastfed infant, breastfeeding is not recommended in patients with smallpox. There are no data on the presence of brincidofovir in human milk, the effects of the drug on the breastfed infant, or on milk production. Brincidofovir is present in animal milk (see Data).

Data

When brincidofovir was administered to lactating rats (4 mg/kg/day or 15 mg/kg twice weekly), brincidofovir was detected in milk but not in the plasma of nursing pups.

8.3 Females and Males of Reproductive Potential

Based on animal data, TEMBEXA may cause fetal harm [see Use in Specific Populations (8.1)].

Pregnancy Testing

Perform pregnancy testing in individuals of childbearing potential before initiation of TEMBEXA [see Dosage and Administration (2.1) and Warnings and Precautions (5.5)].

Contraception

Females

Advise individuals of childbearing potential to use effective contraception during treatment and for at least 2 months after the last dose of TEMBEXA [see Warnings and Precautions (5.5) and Use in Specific Populations (8.1)].

Males

Advise sexually active individuals with partners of childbearing potential to use condoms during treatment and for at least 4 months after last dose of TEMBEXA.

Infertility

Males

Based on testicular toxicity in animal studies, TEMBEXA may irreversibly impair fertility in individuals of reproductive potential [see Nonclinical Toxicology (13.1)].

8.4 Pediatric Use

As in adults, the effectiveness of TEMBEXA in smallpox infected pediatric patients, including neonates, is based solely on efficacy studies in animal models of orthopoxvirus disease. The recommended pediatric dosing regimen is expected to produce brincidofovir exposures that are comparable to those in adults based on a population pharmacokinetic modeling and simulation approach. The dosage for pediatric patients is based on weight [see Dosage and Administration (2.3) and Clinical Pharmacology (12.3)].

There have been 23 pediatric subjects aged 7 months to 17 years who received TEMBEXA in a randomized, placebo-controlled clinical trial. The safety in adult and pediatric subjects treated with TEMBEXA were similar [see Adverse Reactions (6.1)]. An additional 166 pediatric subjects aged 3 months to 18 years of age received TEMBEXA from uncontrolled studies and expanded access. The dosage of TEMBEXA in pediatric patients <3 months of age was based on modeling and simulations [see Clinical Pharmacology (12.3)].

8.5 Geriatric Use

Of the 392 subjects in the controlled clinical studies, 21% were ≥65 years of age and 1% were ≥75 years of age. The nature and severity of adverse events was comparable between subjects older and younger than 65 years. No alteration of dosing is recommended for patients ≥65 years of age [see Clinical Pharmacology (12.3)].

8.6 Renal Impairment

No dosage adjustment of TEMBEXA is required for patients with mild, moderate, or severe renal impairment or patients with end stage renal disease (ESRD) receiving dialysis [see Clinical Pharmacology (12.3)].

8.7 Hepatic Impairment

Perform hepatic laboratory testing in all patients before starting TEMBEXA and while receiving TEMBEXA, as clinically appropriate. No dosage adjustment is required for patients with mild, moderate, or severe hepatic impairment (Child-Pugh Class A, B, or C) [see Warnings and Precautions (5.2), Adverse Reactions (6.1), and Clinical Pharmacology (12.3)].

10 OVERDOSAGE

There is no clinical experience with overdosage of TEMBEXA. In the event of an overdose, monitor patients for adverse effects and provide appropriate supportive care.

11 DESCRIPTION

TEMBEXA (brincidofovir) tablets, 100 mg, for oral use are immediate release film-coated tablets containing the following inactive ingredients: Colloidal Silicon Dioxide, Crospovidone, FD&C Blue #1/Brilliant Blue FCF Aluminum Lake, FD&C Blue #2/Indigo Carmine Aluminum Lake, Magnesium Stearate, Mannitol, Microcrystalline Cellulose, Polyethylene Glycol, Polyvinyl Alcohol, Purified Water, Silicified Microcrystalline Cellulose, Talc and Titanium Dioxide.

TEMBEXA (brincidofovir) oral suspension, 10 mg/mL, is an aqueous based, preserved, orally dosed suspension. The inactive ingredients are: Citric Acid Anhydrous, Lemon Lime Flavor, Microcrystalline Cellulose and Carboxymethyl Cellulose Sodium, Purified Water, Simethicone 30% Emulsion, Sodium Benzoate, Sucralose, Trisodium Citrate Anhydrous, and Xanthan Gum.

Brincidofovir is an orthopoxvirus nucleotide analog DNA polymerase inhibitor and a lipid conjugate of the nucleotide analog cidofovir and is indicated for the treatment of human smallpox disease.

The full chemical name is: Phosphonic acid, P-[[(1S)-2-(4-amino-2-oxo-1(2H)-pyrimidinyl)-1‑(hydroxymethyl)ethoxy]methyl]-, mono[3-(hexadecyloxy)propyl] ester.

The molecular formula of brincidofovir
is C27H52N3O7P and the relative
molecular mass is 561.70.

The structure is shown at right.

Brincidofovir is a white to off‑white
crystalline powder as a free acid
and practically insoluble in water.

12 CLINICAL PHARMACOLOGY

12.1 Mechanism of Action

Brincidofovir is an antiviral drug against variola (smallpox) virus [see Microbiology (12.4)].

12.2 Pharmacodynamics

Brincidofovir and its active metabolite cidofovir diphosphate exposure-response relationships and time course of pharmacodynamic responses are unknown.

Cardiac Electrophysiology

TEMBEXA does not prolong the QT interval at the anticipated therapeutic exposure.

12.3 Pharmacokinetics

Brincidofovir is a prodrug that is converted intracellularly to cidofovir, which is subsequently phosphorylated to cidofovir diphosphate, the active antiviral moiety, following oral administration. Brincidofovir plasma exposures do not accumulate after repeat doses. The metabolite cidofovir diphosphate reaches maximum concentration at 47 hours (23 to 311 hours) following administration of the recommended dose, with a mean (CV%) half-life of 113 hours (34.2%). The pharmacokinetic properties of brincidofovir following administration of TEMBEXA are provided in Table 4. The pharmacokinetic parameters of brincidofovir and cidofovir diphosphate following administration of TEMBEXA at the recommended dose are provided in Table 5.

Table 4: Pharmacokinetic Properties of Brincidofovira
Absorption
Bioavailability | Oral suspension | 16.8%
Bioavailability | Tablet | 13.4%
Tmaxb |  | 3 hours (2 to 8 hours)
Effect of food on TEMBEXA Tablet (relative to fasting)c |  | - AUCinf decreased by 31% - Cmax decreased by 49%
Distribution
% Bound to human plasma proteins |  | >99.9%
Blood-to-plasma ratio (drug or drug-related materials)d |  | 0.48 to 0.61
Apparent Volume of distribution, L |  | 1230
Elimination
Apparent Clearance, L/hr |  | 44.1
Mean terminal half-life (t1/2), hr |  | 19.3
Metabolism
Metabolic pathways |  | hydrolysis, CYP4F2
Metabolites |  | cidofovir and cidofovir diphosphate (active)
Excretion
% of dose excreted in urined |  | 51%, as metabolites
% of dose excreted in fecesd |  | 40%, as metabolites
a. Healthy adults.
b. Administered under fasted conditions.
c. Low-fat meal: ~400 calories, with ~25% calories from fat. No clinically meaningful change in intracellular concentrations of cidofovir diphosphate were seen when TEMBEXA Tablet was administered with a low-fat meal. The effect of food on TEMBEXA oral suspension has not been studied.
d. Following administration of radiolabeled brincidofovir.

Table 5: Single-Dose Pharmacokinetic Parameters of Brincidofovir and Cidofovir Diphosphatea
PK Parameter | Geometric Mean (%CV)
PK Parameter | Brincidofovir | Cidofovir diphosphate
Cmax | 480 ng/mL (70%) | 9.7 pg/10^6 cells (75%)
AUCtau | 3400 ng·hr/mL (58%) | 1200 pg·hr/10^6 cells (75%)
AUC = area under the time concentration curve; Cmax = maximum concentration; CV = coefficient of variation.
a. Healthy adults.

Metabolism

Brincidofovir is metabolized by hydrolysis of the phosphoester bond to form cidofovir. Cidofovir is subsequently phosphorylated to form cidofovir diphosphate. Brincidofovir is also carboxylated at the terminal carbon by Cytochrome P450 (CYP) 4F2, followed by subsequent CYP-mediated oxidations and multiple cycles of fatty acid beta-oxidation. The major inactive metabolites formed via these pathways are CMX103 (3-hydroxypropyl ester of cidofovir) and CMX064 (4‑(3-propoxy)butanoic acid ester of cidofovir).

Genetic and chemical inhibition of acid sphingomyelinase enzyme activity in multiple human cell lines resulted in substantially lower concentrations of cidofovir and cidofovir diphosphate (the active drug), compared to controls with functional acid sphingomyelinase enzyme activity. Findings show acid sphingomyelinase plays a major role in the hydrolysis of brincidofovir to cidofovir in these cell lines. Based on in vitro data, acid sphingomyelinase deficiency may reduce the ability to convert brincidofovir to cidofovir and cidofovir diphosphate; however, the clinical relevance of this finding is unknown.

Comparison of Animal and Human Pharmacokinetic Data to Support Effective Human Dose Selection

Because the effectiveness of TEMBEXA cannot be tested in humans, a comparison of brincidofovir and cidofovir diphosphate exposures achieved in human subjects to those observed in animal models of orthopoxvirus infection (rabbits infected with rabbitpox virus, and mice infected with ectromelia virus) in efficacy studies was necessary to support the dose and regimen of 200 mg once a week for 2 doses for treatment of smallpox disease in humans. Humans achieve greater systemic exposures (AUC and Cmax) of brincidofovir and greater than or equal to intracellular concentrations of cidofovir diphosphate following a 200 mg once a week dose when compared with therapeutic exposure in the animal models [see Clinical Studies (14)].

Specific Populations

No clinically meaningful differences in the pharmacokinetics of brincidofovir were observed based on age, sex, race, reduced activity in the CYP4F2 enzyme, renal impairment including ESRD with or without dialysis (based on estimated glomerular filtration rate [GFR]), or hepatic impairment (Child-Pugh Class B, C).

Patients Requiring Hemodialysis

The AUC and Cmax of brincidofovir and its metabolite cidofovir were comparable between subjects requiring hemodialysis whether on- or off-dialysis.

Pediatric Patients

The pharmacokinetics of TEMBEXA suspension has been evaluated in pediatric individuals. Pharmacokinetic simulation was used to derive dosing regimens that are predicted to provide pediatric patients, including neonates, with exposures comparable to the observed exposure in adults receiving TEMBEXA tablets.

Drug Interaction Studies

Clinical Studies

OATP1B1 and 1B3 Inhibitors: A single 600 mg oral cyclosporine (OATP1B1 and 1B3 inhibitor) dose increased the mean brincidofovir AUC0-inf and Cmax by 374% and 269%, respectively, when administered concomitantly with TEMBEXA.

CYP Substrates: No clinically significant differences in the pharmacokinetics of midazolam (sensitive CYP3A substrate) were observed when administered concomitantly with TEMBEXA.

P-gp Substrates: No clinically significant differences in the pharmacokinetics of dabigatran etexilate (P-gp substrate) were observed when administered concomitantly with TEMBEXA.

In vitro Studies Where Drug Interaction Potential Was Not Further Evaluated Clinically

CYP Enzymes: Brincidofovir is a direct and reversible inhibitor of CYP1A2, CYP2B6, CYP2C8, CYP2C9, CYP2C19, CYP2D6, CYP4F2. Brincidofovir is not an inducer of CYP1A2, CYP2B6 or CYP3A.

Transporter Systems: Brincidofovir is an inhibitor of Breast Cancer Resistance Protein (BCRP), multidrug resistance-associated protein 2 (MRP2), bile salt export pump (BSEP), OATP1B1, Organic Anion Transporter 1 (OAT1), and OAT3. Brincidofovir is not an inhibitor of OATP1B3, Organic Cation Transporter 2 (OCT2), multidrug and toxin extrusion protein 1 (MATE1), or MATE2-K in vitro.

12.4 Microbiology

Mechanism of Action

Brincidofovir is a lipid conjugate of cidofovir, an acyclic nucleotide analog of deoxycytidine monophosphate. The lipid conjugate is designed to mimic a natural lipid, lysophosphatidylcholine, and thereby use endogenous lipid uptake pathways. Once inside cells, the lipid ester linkage of brincidofovir is cleaved to liberate cidofovir, which is then phosphorylated to produce the active antiviral, cidofovir diphosphate. Based on biochemical and mechanistic studies using recombinant vaccinia virus E9L DNA polymerase, cidofovir diphosphate selectively inhibits orthopoxvirus DNA polymerase-mediated viral DNA synthesis. Incorporation of cidofovir into the growing viral DNA chain results in reductions in the rate of viral DNA synthesis.

Activity in Cell Culture

The median 50% effective concentration (EC50) of brincidofovir against variola virus was 0.11 µM (range 0.05 to 0.21 µM) across 5 variola virus strains chosen to represent 5 distinct variola virus DNA polymerase genotypes. The median EC50 values of brincidofovir against rabbitpox, ectromelia, vaccinia, and monkeypox viruses were 1.10 µM (n=4, 0.5-1.89 µM), 0.33 µM (n=5, 0.12-0.51 µM), 0.17 µM (n=22, 0.004-1.2 µM), and 0.074 µM (n=2, 0.023-0.12 µM), respectively.

Non-antagonistic antiviral activity of brincidofovir and tecovirimat has been demonstrated in cell culture and animal models.

Resistance

There are no known instances of naturally occurring brincidofovir resistant orthopoxviruses, although brincidofovir resistance may develop under drug selection. Cell culture studies have shown that certain amino acid substitutions in the target viral DNA polymerase protein can confer reductions in brincidofovir antiviral activity. The possibility of resistance to brincidofovir should be considered in patients who either fail to respond to therapy or who develop recrudescence of disease after an initial period of responsiveness.

Cross-resistance

Cross-resistance between brincidofovir and tecovirimat is not expected based on their distinct mechanisms of action. Where tested, orthopoxvirus isolates resistant to tecovirimat have not been resistant to brincidofovir and/or cidofovir and vice versa.

13 NONCLINICAL TOXICOLOGY

13.1 Carcinogenesis, Mutagenesis, Impairment of Fertility

Carcinogenesis and Mutagenesis

Palpable masses occurred in rats with high frequency after as few as 26 oral doses of brincidofovir at systemic exposures less than the expected human exposure based on the recommended dose of TEMBEXA. The masses diagnosed as mammary adenocarcinomas, carcinoma in squamous cell, Zymbal’s gland, uterus and small intestine and hemangiosarcomas in mesenteric and mediastinal lymph node, liver and abdominal cavity were observed in rats following long term (13-weeks and 26-weeks) dosing studies. No tumors occurred in rats after 9 twice-weekly intravenous doses, although rats were only followed for 14 days after the last administration. Based on these data and the unknown translation of nonclinical findings to clinical risk, TEMBEXA is considered a potential human carcinogen.

Brincidofovir was negative in a bacterial mutagenicity (Ames) assay and an in vivo micronucleus assay in mice. Brincidofovir was positive for increased structural chromosomal aberrations in the absence of metabolic activation in an in vitro assay.

Impairment of Fertility

In chronic dosing studies with orally administered brincidofovir, testicular effects were seen in both rats and monkeys. Monkeys administered twice weekly doses of brincidofovir via oral gavage for 9 months exhibited atrophy of the seminiferous tubules and hypospermia in the epididymides. Based on sperm analysis and histopathology, these findings demonstrated a trend towards recovery after a 6 month, post-dosing period. Rats administered brincidofovir via oral gavage twice weekly for 13 weeks exhibited decreased testes weights, depletion of spermatogenesis and hypospermia. Unlike in the monkey, recovery was not demonstrated in the rats following a 12-week post-dosing period.

In a rat fertility and early embryonic development study, administration of brincidofovir once daily beginning 15 days before cohabitation, during cohabitation and continuing through gestation day 7 resulted in decreased embryonal viability at 0.25 mg/kg/day, a dose that did not cause maternal toxicity. Male rats dosed twice weekly by oral gavage for 10 to 19 weeks had reduced sperm motility and a decrease in total sperm count. These effects resulted in reduced fertility during the first cohabitation period, and infertility during the second cohabitation period.

Brincidofovir exposures in both monkeys and rats were less than exposures seen in humans administered 200 mg brincidofovir. Studies conducted using intravenous brincidofovir to achieve clinically relevant exposures demonstrated diminished but ongoing spermatogenesis in the tubules of rats 15 weeks after administration of 3 doses of brincidofovir administered once weekly. The testicular pathology appears to be an effect on the mitotic spermatogonia.

13.2 Animal Toxicology and/or Pharmacology

Gastrointestinal Toxicity: GI toxicity is the dose-limiting toxicity of orally-administered brincidofovir. Signs of GI toxicity include decreased body weight and food consumption, fecal changes (absent, nonformed, or liquid feces), and dehydration. Dose-limiting GI events, diagnosed as gastropathy and enteropathy or enteritis, were observed following daily oral administration of brincidofovir in mice and monkeys. A single dose study to characterize the pathological dynamics of GI toxicity and potential reversibility revealed a dose responsive enteritis in rats, which reversed in surviving animals by 14 days post-dose. Subsequent animal studies used twice weekly oral administration to reflect anticipated clinical use and no dose-limiting GI toxicity was observed.

Aminotransferase Elevations: Increases in ALT (2- to 5-fold) were observed in both rodent and nonrodent species in nonclinical toxicology studies of orally administered brincidofovir. The changes seen with oral dosing appeared with highest frequency in monkeys, followed by mice and then rats. ALT elevations did not correlate with dose concentration and reversed after cessation of dosing. There were no gross or microscopic hepatic changes that correlated with the ALT increases.

14 CLINICAL STUDIES

Overview

The effectiveness of TEMBEXA for treatment of smallpox disease has not been determined in humans because adequate and well-controlled field trials have not been feasible and inducing smallpox disease in humans to study the efficacy of the drug is not ethical. Therefore, the effectiveness of TEMBEXA for treatment of smallpox disease was established based on results of adequate and well-controlled animal efficacy studies of rabbits and mice infected with species specific non-variola orthopoxviruses. Survival rates observed in the animal studies may not be predictive of survival rates in clinical practice.

Study Design

Efficacy studies were conducted in the rabbitpox model (New Zealand White rabbits infected with rabbitpox virus) and the mousepox model (BALB/c mice infected with ectromelia virus).

The primary efficacy endpoint for these studies was survival. Survival was monitored for 4 to 5 times the mean time to death for untreated animals in each model.

In the rabbitpox study, rabbits were lethally challenged intradermally with 600 plaque-forming units of rabbitpox virus; brincidofovir was administered orally with a regimen of 20/5/5 mg/kg (administered every 48 hours for 3 doses) with brincidofovir treatment initiated on 3, 4, 5, or 6 days post-challenge. The timing of brincidofovir dosing was intended to assess efficacy when treatment is initiated after animals have developed clinical signs of disease, specifically fever in rabbits. Clinical signs of disease were evident in some animals at Day 3 post-challenge but were evident in all animals by Day 4 post-challenge.

In the mousepox study, mice were lethally challenged intranasally with 200 plaque-forming units of ectromelia virus; brincidofovir was administered orally with a regimen of 20/5/5 mg/kg or 10/5/5 mg/kg (administered every 48 hours for 3 doses) with brincidofovir treatment initiated on 4, 5, 6, or 7 days post-challenge. All animals had detectable viremia by 4 days post-challenge. In the mousepox model, a clinically evident sign of disease could not be identified to use as a trigger to initiate treatment.

Study Results

Treatment with brincidofovir resulted in statistically significant improvement in survival relative to placebo, except when the 10/5/5 mg/kg regimen was initiated at Day 6 post-challenge in the mousepox study (Table 6).

Table 6: Survival Rates in Brincidofovir Treatment Studies in the Rabbitpox and Mousepox Models
Dose Regimen (mg/kg) | Treatment Initiation Day | Survival % (# survived/n) |  | Survival Rate Difference; (95% CI)a | p-valueb
Dose Regimen (mg/kg) | Treatment Initiation Day | Placebo | Brincidofovir | Survival Rate Difference; (95% CI)a | p-valueb
Rabbitpoxc
Study 1 | Day 4 | 29%; (8/28) | 90% (26/29) | 61% (36%, 79%) | <0.0001
Study 1 | Day 5 | 29%; (8/28) | 69% (20/29) | 40% (12%, 63%) | 0.0014
Study 1 | Day 6 | 29%; (8/28) | 69% (20/29) | 40% (12%, 63%) | 0.0014
Mousepoxd
Study 2 | Day 4 | 13%; (4/32) | 78% (25/32) | 66% (44%, 82%) | <0.0001
Study 2 | Day 5 | 13%; (4/32) | 66% (21/32) | 53% (29%, 72%) | <0.0001
Study 2 | Day 6 | 13%; (4/32) | 34% (11/32) | 22% (1%, 43%) | 0.0233e
a. Survival percentage with brincidofovir-treated animals minus survival percentage in placebo-treated animals. Exact confidence intervals are presented.
b. P-value is from 1-sided Boschloo test compared with placebo.
c. 20/5/5 mg/kg (fully effective dose in the rabbitpox model)
d. 10/5/5 mg/kg (fully effective dose in the mousepox model)
e. P-value is not significant at the one-sided alpha of 0.0125.

16 HOW SUPPLIED/STORAGE AND HANDLING

TEMBEXA Tablets:

Tablets are blue, modified-oval shape, film-coated tablets debossed with BCV on one side and 100 on the other side and packaged into blister cards. Each blister cavity contains one film-coated tablet containing 100 mg of brincidofovir. The blister card is placed in a child-resistant wallet. Each wallet (NDC 64678-010-01) contains one (1) blister card with a total of 4 film-coated tablets.

Store at 20°C to 25°C (68°F to 77°F); excursions permitted from 15°C to 30°C (59°F to 86°F) [see USP Controlled Room Temperature].

Do not divide, break, or crush the tablets. Avoid direct contact with broken or crushed tablets. If contact with skin or mucous membranes occurs, wash thoroughly with soap and water, and rinse eyes thoroughly with water [see Warnings and Precautions (5.6)].

TEMBEXA Oral Suspension:

Aqueous based, preserved white to off-white opaque, lemon lime flavored suspension containing 10 mg/mL of brincidofovir (NDC 64678-012-01) packaged into a high density polyethylene bottle with a low density polyethylene press-in bottle adaptor (PIBA) inserted into the bottle. The bottle is capped by a child-resistant closure. Each bottle is filled to deliver 65 mL of brincidofovir.

Store at 20°C to 25°C (68°F to 77°F); excursions permitted from 15°C to 30°C (59°F to 86°F) [see USP Controlled Room Temperature]. Do not freeze.

Avoid direct contact with oral suspension. If contact with skin or mucous membranes occurs, wash thoroughly with soap and water, and rinse eyes thoroughly with water [see Warnings and Precautions (5.6)].

17 PATIENT COUNSELING INFORMATION

Advise the patient to read the FDA-approved patient labeling (Patient Information).

Efficacy Based on Animal Models Alone

Inform patients that the efficacy of TEMBEXA is based solely on efficacy studies demonstrating a survival benefit in animals and that the effectiveness of TEMBEXA has not been tested in humans with smallpox disease [see Clinical Studies (14)].

Elevations of Hepatic Transaminases and Bilirubin

Inform patients of the need for liver monitoring before treatment with TEMBEXA and during treatment if signs or symptoms of liver injury occur. Advise patients to report symptoms that may indicate liver injury, including right upper abdominal discomfort, dark urine, or jaundice [see Warnings and Precautions (5.2)].

Diarrhea and Other Gastrointestinal Adverse Events

Inform patients of the risk of diarrhea and other GI adverse events (nausea, vomiting, and abdominal pain) while taking TEMBEXA. Advise patients to inform their healthcare provider if they develop severe diarrhea or other severe GI symptoms [see Warnings and Precautions (5.3) and Adverse Reactions (6.1)].

Important Drug Interactions

Inform patients that TEMBEXA may interact with some drugs. If concomitant use of OATP1B1 and 1B3 inhibitors with TEMBEXA is necessary, advise patients to postpone the dosing of these medicines for at least 3 hours after TEMBEXA administration [see Drug Interactions (7.1) and Clinical Pharmacology (12.3)].

Embryo-fetal Toxicity

Advise pregnant individuals and individuals of childbearing potential of the risk to a fetus and to inform their healthcare provider of a known or suspected pregnancy. Advise individuals of childbearing potential to use effective contraception during treatment with TEMBEXA and for at least 2 months after the last dose. Due to animal findings of testicular toxicity, advise individuals of reproductive potential with partners of childbearing potential to use condoms during treatment with TEMBEXA and for at least 4 months after the last dose [see Warnings and Precautions (5.5, 5.7) and Use in Specific Populations (8.3)].

Infertility

Advise individuals of reproductive potential that treatment with TEMBEXA may deplete sperm, resulting in infertility [see Use in Specific Populations (8.3) and Nonclinical Toxicology (13.1)].

Lactation

Instruct individuals with smallpox not to breastfeed their infant because of the risk of passing variola virus to the breastfed infant [see Use in Specific Populations (8.2)].

Important Administration Instructions for Oral Suspension

Instruct patients or caregivers to use an oral dosing syringe to correctly measure the prescribed amount of medication. Oral dosing syringes may be obtained from the pharmacy. Refer to instructions above for administration of TEMBEXA oral suspension through enteral tubes [see Dosage and Administration (2.2)].

Advise patients taking the oral suspension to discard unused portion after completion of the 2 prescribed doses.

Handling

Advise patients not to divide, break, or crush tablets. Advise patients to avoid direct contact with broken or crushed tablets and oral suspension. If contact with skin or mucous membranes occurs, inform patients to wash thoroughly with soap and water, and rinse eyes thoroughly with water [see Dosage and Administration (2.2) and How Supplied/Storage and Handling (16)].

Manufactured for Emergent BioDefense
Operations Lansing LLC

3500 North Martin Luther King Jr Blvd
Lansing, MI 48906

Patient Package Insert

PATIENT INFORMATION

TEMBEXA (tem-BEKS-uh)
(brincidofovir)
tablets

TEMBEXA (tem-BEKS-uh)
(brincidofovir)
oral suspension

What is TEMBEXA?

TEMBEXA is a prescription medicine used to treat smallpox disease caused by a type of virus called variola virus in adults, children, and infants.

- The effectiveness of TEMBEXA has been studied only in animals with orthopoxvirus diseases. There have been no human studies in people who have smallpox disease.
- The safety of TEMBEXA has been studied in adults and children older than 3 months.
- TEMBEXA may not work in people who have a weakened immune system.
- The safety and effectiveness of TEMBEXA is not known for diseases other than human smallpox disease.

Before taking TEMBEXA, tell your healthcare provider about all your medical conditions, including if you:

- are pregnant or plan to become pregnant. TEMBEXA can harm your unborn baby. Tell your healthcare provider if you become pregnant or think that you may be pregnant during treatment with TEMBEXA.
  - Your healthcare provider should check to see if you are pregnant before you begin treatment with TEMBEXA.
  - Your healthcare provider may use another medicine to treat your smallpox if you are pregnant.
  - Individuals who can get pregnant should use effective birth control during treatment with TEMBEXA and for at least 2 months after the last dose.
  - TEMBEXA may harm your sperm. If you are sexually active with an individual who can become pregnant, you should use condoms during treatment with TEMBEXA and for at least 4 months after the last dose.
- are breastfeeding or plan to breastfeed. Breastfeeding is not recommended for individuals with smallpox because of the risk of passing variola virus to the breastfed infant.

Tell your healthcare provider about all the medicines you take, including prescription and over-the-counter medicines, vitamins, and herbal supplements. Some medicines interact with TEMBEXA causing side effects. Keep a list of your medicines to show your healthcare provider and pharmacist.

- You can ask your healthcare provider or pharmacist for a list of medicines that interact with TEMBEXA.
- Do not start taking a new medicine without telling your healthcare provider. Your healthcare provider can tell you if it is safe to take TEMBEXA with other medicines.

How should I take TEMBEXA?

- Take TEMBEXA exactly as your healthcare provider tells you.
- It is important to take TEMBEXA one time a week for 2 doses (on Day 1 and Day 8), as instructed. Do not miss or skip a dose of TEMBEXA.
- TEMBEXA tablets can be taken on an empty stomach or with a low-fat meal (around 400 calories, with about 25% of calories from fat). Talk to your healthcare provider about examples of foods that you can eat for a low-fat meal.
- TEMBEXA oral suspension can be taken on an empty stomach.
- For adults and children taking the TEMBEXA oral suspension, shake the suspension bottle well before each use. Use an oral dosing syringe to correctly measure your dose. Ask your pharmacist for an oral dosing syringe if you do not have one. Only take the amount prescribed to you. Throw away (discard) any unused portion.
- For people who are not able to swallow: You may give TEMBEXA oral suspension through a naso-gastric (NG) or gastrostomy (“g”) tube to someone who is not able to swallow, using the following instructions:
  - Draw up the prescribed amount (dose) of TEMBEXA oral suspension using a catheter-tip syringe with mL markings on it.
  - Give the dose through the naso-gastric tube or gastrostomy tube.
  - Refill the catheter-tip syringe with 3 mL of water and shake the syringe. Give the contents of the syringe through the naso-gastric tube or gastrostomy tube.
  - Flush with water before and after administration.
- Stay under the care of your healthcare provider during treatment with TEMBEXA.
- Do not change your dose or stop taking TEMBEXA without talking to your healthcare provider.
- Swallow TEMBEXA tablets whole. Do not divide, break, or crush TEMBEXA tablets. Do not touch broken or crushed tablets or oral suspension. If you touch TEMBEXA, wash your hands very well with soap and water. If you get TEMBEXA in your eyes, rinse your eyes well with water.
- If you take too much TEMBEXA, call your healthcare provider or go to the nearest hospital emergency room right away.

What are the possible side effects of TEMBEXA?

TEMBEXA may cause serious side effects, including:

- Liver problems. Your healthcare provider should perform blood tests to check your liver before you start taking TEMBEXA and during treatment with TEMBEXA for any signs or symptoms of liver problems. Call your healthcare provider right away if you have the following symptoms:
  - Stomach discomfort in the upper right side
  - Dark urine
  - Yellowing of your skin or the whites of your eyes (jaundice)
- Diarrhea. Diarrhea is common in people who take TEMBEXA but can also be serious. Call your healthcare provider right away if you develop diarrhea with 4 or more stools per day over your usual daily number of stools.

The most common side effects of TEMBEXA include:

- Diarrhea
- Nausea
- Stomach pain
- Vomiting

TEMBEXA may cause low sperm counts and affect the ability to conceive children. Talk to your healthcare provider if you have concerns about fertility.

These are not all the possible side effects of TEMBEXA. Call your doctor for medical advice about side effects. You may report side effects to FDA at 1-800-FDA-1088.

How should I store TEMBEXA?

- Store TEMBEXA tablets and oral suspension at room temperature between 68°F to 77°F (20°C to 25°C).
- Do not freeze TEMBEXA oral suspension.
- Keep TEMBEXA in its original container.

Keep TEMBEXA and all other medicines out of the reach of children.

General information about the safe and effective use of TEMBEXA.

Medicines are sometimes prescribed for purposes other than those listed in a Patient Information leaflet. Do not use TEMBEXA for a condition for which it was not prescribed. Do not give TEMBEXA to other people, even if they have the same symptoms that you have. It may harm them. You can ask your pharmacist or healthcare provider for information about TEMBEXA that is written for health professionals.

What are the ingredients in TEMBEXA?

Active ingredient: brincidofovir

Inactive ingredients:

- Tablets: Colloidal Silicon Dioxide, Crospovidone, FD&C Blue #1/Brilliant Blue FCF Aluminum Lake, FD&C Blue #2/Indigo Carmine Aluminum Lake, Magnesium Stearate, Mannitol, Microcrystalline Cellulose, Polyethylene Glycol, Polyvinyl Alcohol, Purified Water, Silicified Microcrystalline Cellulose, Talc, Titanium Dioxide.
- Oral Suspension: Citric Acid Anhydrous, Lemon Lime Flavor, Microcrystalline Cellulose and Carboxymethyl Cellulose Sodium, Purified Water, Simethicone 30% Emulsion, Sodium Benzoate, Sucralose, Trisodium Citrate Anhydrous, Xanthan Gum.

Manufactured for Emergent BioDefense Operations Lansing LLC

3500 North Martin Luther King Jr Blvd
Lansing, MI 48906

For more information, call 1-877-246-8472.

This Patient Information has been approved by the U.S. Food and Drug Administration. Issued: 10/2022

PACKAGE/LABEL PRINCIPAL DISPLAY PANEL

Tembexa bricidofovir, 100 mg per tablet, Rx Only, For oral use, Contents: 4 Tablets, See full prescribing information for Tembexa inside.

Tembexa (brincidofovir) 100 mg per tablet

NDC 64678-010-01
Manufactured for
Emergent BioDefense Operations Lansing LLC